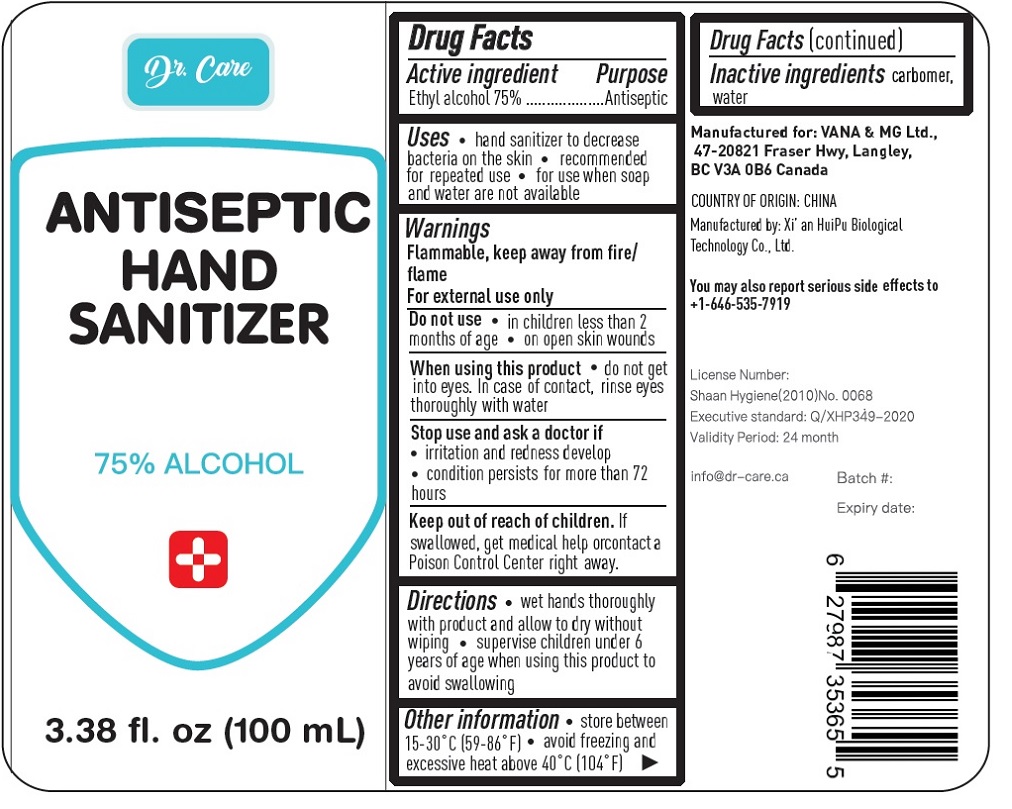 DRUG LABEL: Dr. Care ANTISEPTIC HAND SANITIZER
NDC: 76950-101 | Form: LIQUID
Manufacturer: Vana & Mg Ltd
Category: otc | Type: HUMAN OTC DRUG LABEL
Date: 20200429

ACTIVE INGREDIENTS: ALCOHOL 75 mL/100 mL
INACTIVE INGREDIENTS: CARBOMER HOMOPOLYMER, UNSPECIFIED TYPE; WATER

Dr. Care ANTISEPTIC HAND SANITIZER

Active ingredient

Ethyl alcohol 75%

Purpose

Antiseptic

INDICATIONS AND USAGE

Uses • hand sanitizer to decrease bacteria on the skin • recommended for repeated use • for use when soap and water are not available

Warnings

Flammable. Keep away from fire/flame.

For external use only

Do not use • in children less than 2 months of age • on open skin wounds

When using this product • do not get into eyes. In case of contact, rinse eyes thoroughly with water

Stop use and ask a doctor if

• irritation and redness develop

• condition persists for more than 72 hours

Keep out of reach of children. If swallowed, get medical help or contact a Poison Control Center right away.

DOSAGE AND ADMINISTRATION

Directions • Wet hands thoroughly with product and allow to dry without wiping. • supervise children under 6 years of age when using this product to avoid swallowing

Other information • store between 15-30° C (59-86°F) • avoid freezing and excessive heat above 40° C (104° F)

Inactive ingredients carbomer, water

75% ALCOHOL

Manufactured for: VANA & MG Ltd.,

47-20821 Fraser Hwy, Langley

BC V3A 0B6 Canada

COUNTRY OF ORIGIN: CHINA

Manufactured by: Xi' HuiPu Biological Technology Co. Ltd.

You may also report serious side effects to +1-646-535-7919

Licence Number: Shaan Hygiene(2010)No. 0068

Executive standard: Q/XHP349-2020

Validity Period: 24 month

info@dr-care.ca